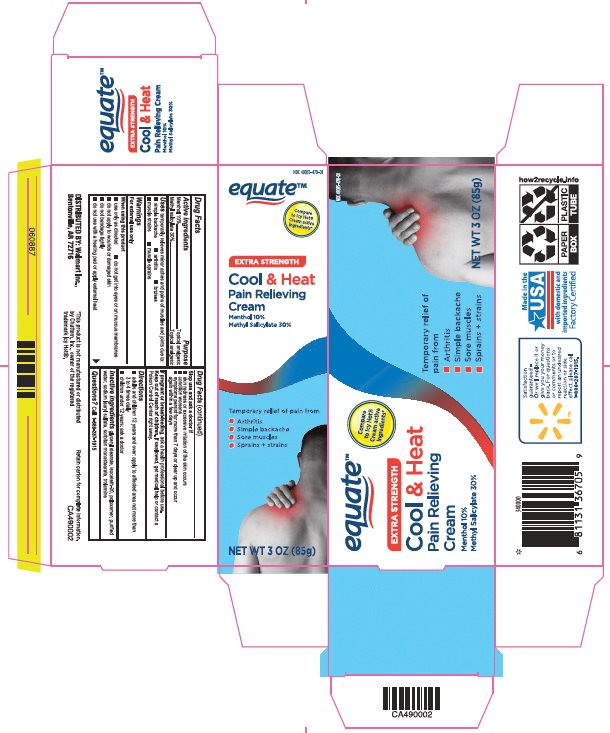 DRUG LABEL: Equate Cool and Heat
NDC: 49035-470 | Form: CREAM
Manufacturer: Wal-Mart Stores Inc
Category: otc | Type: HUMAN OTC DRUG LABEL
Date: 20241217

ACTIVE INGREDIENTS: MENTHOL, UNSPECIFIED FORM 100 mg/1 g; METHYL SALICYLATE 300 mg/1 g
INACTIVE INGREDIENTS: GLYCERYL MONOSTEARATE; ISOCETETH-20; POLOXAMER 407; WATER; SODIUM LAURYL SULFATE; SORBITAN MONOSTEARATE; TROLAMINE

Drug Facts - Equate Cool and Heat

Active ingredient

Menthol 10%

Methyl salicylate 30%

Purpose

Menthol - Topical analgesic

Methyl salicylate - Topical analgesic

Uses

temporarily relieves minor aches and pains of muscles and joints due to:

- simple backache
- arthritis
- bruises
- muscle strains
- muscle sprains

Warnings

For external use only

When using this product

- use only as directed
- do not get into eyes or on mucous membranes
- do not apply to wounds or damaged skin
- do not bandage tightly
- do not use with a heating pad or apply external heat

Stop use and ask a doctor if

- skin redness or excessive irritation of the skin occurs
- condition worsens
- symptoms persist for more than 7 days or clear up and occur again within a few days

If pregnant or breast-feeding,

ask a health professional before use.

Keep Out of Reach of Children

If swallowed, get medical help or contact a Poison Control Center right away.

Directions

- adults and children 12 years and over: apply to affected area not more than 3 to 4 times daily
- children under 12 years: ask a doctor

Inactive Ingredients

glyceryl stearate, isoceteth-20, poloxamer, purified water, sodium lauryl sulfate, sorbitan monostearate, trolamine

Questions

Call: 1-888-287-1915